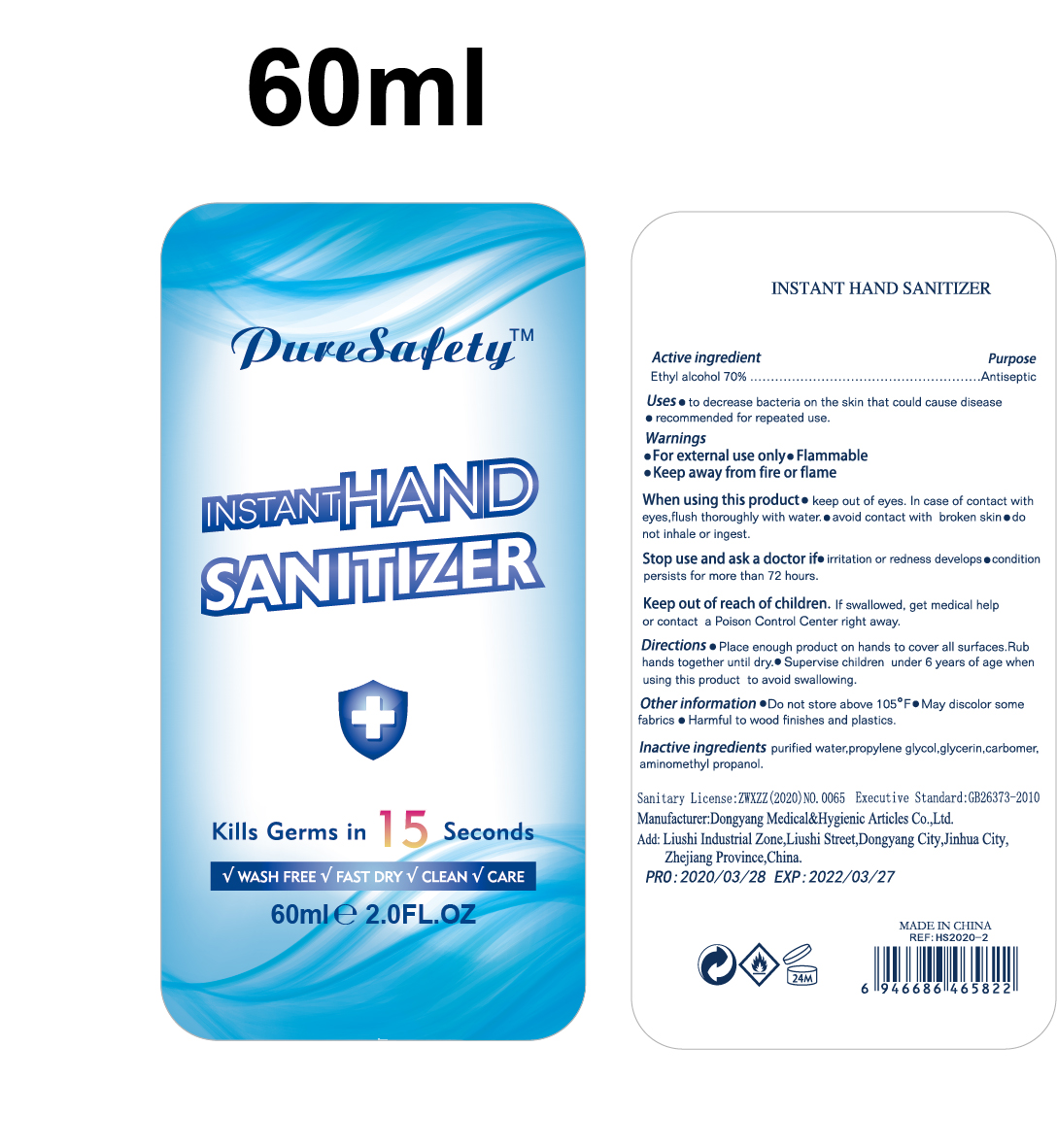 DRUG LABEL: INSTANT HAND SANITIZER
NDC: 81276-003 | Form: LIQUID
Manufacturer: Dongyang Medical & Hygienic Articles Co., Ltd.
Category: otc | Type: HUMAN OTC DRUG LABEL
Date: 20201223

ACTIVE INGREDIENTS: ALCOHOL 42 mL/60 mL
INACTIVE INGREDIENTS: AMINOMETHYLPROPANOL; GLYCERIN; CARBOMER HOMOPOLYMER, UNSPECIFIED TYPE; WATER; PROPYLENE GLYCOL

81276-003 60ml gel

This is a hand sanitizer manufactured according to the Temporary Policy for Preparation of Certain Alcohol-Based Hand Sanitizer Products During the Public Health Emergency (CoViD-19); Guidance for Industry.

The hand sanitizer is manufactured using only the following United States Pharmacopoeia (USP) grade ingredients in the preparation of the product (percentage in final product formulation) consistent with World Health Organization (WHO) recommendations:

1. Alcohol (ethanol) (USP or Food Chemical Codex (FCC) grade) (80%, volume/volume (v/v)) in an aqueous solution denatured according to Alcohol and Tobacco Tax and Trade Bureau regulations in 27 CFR part 20.
2. Glycerol (1.45% v/v).
3. Hydrogen peroxide (0.125% v/v).
4. Sterile distilled water or boiled cold water.

The firm does not add other active or inactive ingredients. Different or additional ingredients may impact the quality and potency of the product.

Active Ingredient(s)

Alcohol 70% v/v. Purpose: Antiseptic

Purpose

Antiseptic, Hand Sanitizer

Use

- to decrease bacteria on the skin that could cause disease.
- recommended for repeated use.

Warnings

- For external use only. Flammable.
- Keep away from heat or flame.

Do not use

- in children less than 2 months of age
- on open skin wounds

When using this product:

- keep out of eyes. In case of contact with eyes, flush thoroughly with water.

- avoid contact with broken skin
- do not inhale or ingest.

Stop use and ask a doctor:

- if irritation or redness develops.
- condition persists for more than 72 hours.

Keep out of reach of children. If swallowed, get medical help or contact a Poison Control Center right away.

Directions

- Place enough product on hands to cover all surfaces. Rub hands together until dry.
- Supervise children under 6 years of age when using this product to avoid swallowing.

Inactive ingredients

purified water,Propylene Glycol,Glycerin, CARBOMER, AMINOMETHYL PROPANOL

Package Label - Principal Display Panel

60 mL NDC: 81276-003-01